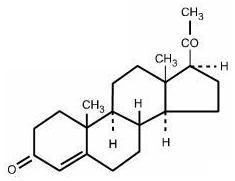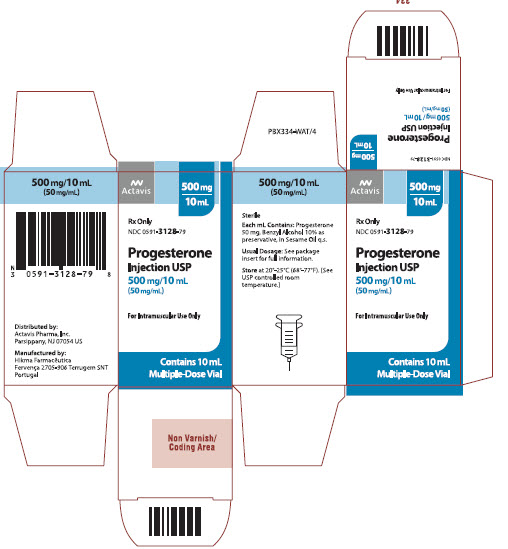 DRUG LABEL: PROGESTERONE
NDC: 0591-3128 | Form: INJECTION, SOLUTION
Manufacturer: Actavis Pharma, Inc.
Category: prescription | Type: HUMAN PRESCRIPTION DRUG LABEL
Date: 20221005

ACTIVE INGREDIENTS: PROGESTERONE 50 mg/1 mL
INACTIVE INGREDIENTS: BENZYL ALCOHOL; SESAME OIL

PROGESTERONE INJECTION USP
IN SESAME OIL
FOR INTRAMUSCULAR USE ONLY
Rx only
Revised: September 2014

DESCRIPTION

Progesterone injection, a progestin, is a sterile solution of progesterone in a suitable vegetable oil available for intramuscular use.

Progesterone occurs as a white or creamy white, crystalline powder. It is odorless and is stable in air. Practically insoluble in water, it is soluble in alcohol, acetone, and dioxane and sparingly soluble in vegetable oils.

It has the following structural formula:

C21H30O2 M.W. 314.47

Pregn-4-ene-3, 20-dione

Each mL contains: Progesterone 50 mg, Benzyl Alcohol 10% as preservative in Sesame Oil q.s.

CLINICAL PHARMACOLOGY

Transforms proliferative endometrium into secretory endometrium.

Inhibits (at the usual dose range) the secretion of pituitary gonadotropins, which in turn prevents follicular maturation and ovulation.

Pharmacokinetics and Metabolism:

Absorption: After intramuscular administration of 10 mg of progesterone in oil, maximum plasma concentrations (geometric mean of 7 ng/mL) were reached within approximately 8 hours after injection and plasma concentrations remained above baseline for about 24 hours after injection. Injection of 10, 25, and 50 mg resulted in geometric mean values for maximum plasma concentration (CMAX) of 7, 28, and 50 ng/mL, respectively.

Distribution: Progesterone is extensively bound to plasma proteins, primarily albumin (50-54%) and cortisol-binding protein (43-48%).

Metabolism: Progesterone is metabolized primarily in the liver by reduction to pregnanediol, pregnanetriol, and pregnanolone. Subsequent conjugation results in the formation of glucuronide and sulfate metabolites. The mean plasma metabolic clearance rate in cycling women is 2510 ± 135 (SEM) L/day.

Excretion: The glucuronide and sulfate conjugates of pregnanediol and pregnanolone are excreted in the urine and bile. Progesterone metabolites which are excreted in the bile may undergo enterohepatic recycling or may be excreted in the feces.

The pharmacokinetic data was determined in a small number of patients, limiting the precision in which population values may be estimated.

Special Populations:

Renal Insufficiency: The safety and effectiveness in patients with renal insufficiency have not been established. Since progesterone metabolites are excreted mainly by the kidneys, progesterone should be administered with caution and careful monitoring in this patient population (see PRECAUTIONS).

Hepatic Insufficiency: The safety and effectiveness in patients with hepatic insufficiency have not been established. Since progesterone is metabolized by the liver, use in patients with liver dysfunction or disease is contraindicated (see CONTRAINDICATIONS).

Drug Interactions:

The metabolism of progesterone by human liver microsomes was inhibited by ketoconazole (IC50 < 01 μM). Ketoconazole is a known inhibitor of cytochrome P450 3A4 and these data suggest that ketoconazole or other known inhibitors of this enzyme may increase the bioavailability of progesterone. The clinical relevance of the in vitro findings is unknown.

INDICATIONS AND USAGE

This drug is indicated in amenorrhea and abnormal uterine bleeding due to hormonal imbalance in the absence of organic pathology, such as submucous fibroids or uterine cancer.

CONTRAINDICATIONS

- Current or past history of thrombophlebitis, thromboembolic disorders, or cerebral apoplexy.
- Liver dysfunction or disease.
- Known or suspected malignancy of breast or genital organs.
- Undiagnosed vaginal bleeding.
- Missed abortion.
- Known sensitivity to progesterone injection.
- Known sensitivity to sesame oil/seeds.

WARNINGS

The physician should be alert to the earliest manifestations of thrombotic disorders (thrombophlebitis, cerebrovascular disorders, pulmonary embolism, and retinal thrombosis). Should any of these occur or be suspected, the drug should be discontinued immediately.

Medication should be discontinued pending examination if there is a sudden partial or complete loss of vision, or if there is a sudden onset of proptosis, diplopia or migraine. If examination reveals papilledema or retinal vascular lesions, medication should be withdrawn.

Acute eosinophilic pneumonia has been reported in patients receiving progesterone in sesame oil. In reported cases associated with progesterone in sesame oil, patients developed fever, dyspnea with hypoxic respiratory insufficiency, and diffuse pulmonary infiltrates. In general, patients developed eosinophilic pneumonia 2 to 4 weeks after starting progesterone in sesame oil and improved when progesterone in sesame oil was discontinued and a different formulation of progesterone and/or steroid therapy was initiated. Patients who develop these signs and symptoms while receiving progesterone in sesame oil should undergo prompt medical evaluation, and progesterone in sesame oil should be discontinued immediately.

PRECAUTIONS

General

The pretreatment physical examination should include special reference to breast and pelvic organs, as well as a Papanicolaou smear.

Because progestational drugs may cause some degree of fluid retention, conditions which might be influenced by this condition, such as epilepsy, migraine, asthma, cardiac, or renal dysfunction, require careful observation.

In cases of breakthrough bleeding, as in all cases of irregular bleeding per vaginum, nonfunctional causes should be borne in mind, and adequate diagnostic measures undertaken.

Patients who have a history of psychic depression should be carefully observed and the drug discontinued if the depression recurs to a serious degree.

The age of the patient constitutes no absolute limiting factor although treatment with progestin may mask the onset of the climacteric.

The pathologist should be advised of progestin therapy when relevant specimens are submitted.

There are possible risks which may be associated with the use of progestin treatment, including adverse effects on carbohydrate and lipid metabolism. The dosage used may be important in minimizing these adverse effects.

A decrease in glucose tolerance has been observed in a small percentage of patients on estrogen-progestin combination treatment. The mechanism of this decrease is obscure. For this reason, diabetic patients should be carefully observed while receiving such therapy.

Carcinogenesis, Mutagenesis, Impairment of Fertility

Long-term intramuscular administration of Medroxyprogesterone acetate (MPA) has been shown to produce mammary tumors in beagle dogs. There is no evidence of a carcinogenic effect associated with the oral administration of MPA to rats and mice.

Medroxyprogesterone acetate was not mutagenic in a battery of in vitro or in vivo genetic toxicity assays.

Progesterone at high doses is an antifertility drug and high doses would be expected to impair fertility until the cessation of treatment.

Geriatric Use:

The safety and effectiveness in geriatric patients (over age 65) have not been established.

Pediatric Use:

Safety and effectiveness in pediatric patients have not been established.

Nursing Mothers:

Detectable amounts of drug have been identified in the milk of mothers receiving progestational drugs. The effect of this on the nursing infant has not been determined.

ADVERSE REACTIONS

Breakthrough bleeding; spotting; change in menstrual flow; amenorrhea; edema; change in weight (increase or decrease); changes in cervical erosion and cervical secretions; cholestatic jaundice; breast tenderness and galactorrhea; pain, irritation, and/or redness at the injection area; skin sensitivity reactions consisting of urticaria, pruritus, edema and generalized rash; acne, alopecia and hirsutism; rash (allergic) with and without pruritus; anaphylactoid reactions (including eosinophilic pneumonia); mental depression; pyrexia; insomnia; nausea; and somnolence.

A statistically significant association has been demonstrated between use of estrogen-progestin combination drugs and pulmonary embolism and cerebral thrombosis and embolism. For this reason patients on progestin therapy should be carefully observed. There is also evidence suggestive of an association with neuro-ocular lesions, e.g., retinal thrombosis and optic neuritis.

The following adverse reactions have been observed in patients receiving estrogen-progestin combination drugs: rise in blood pressure in susceptible individual, premenstrual syndrome, changes in libido, changes in appetite, cystitis-like syndrome, headache, nervousness, fatigue, backache, hirsutism, loss of scalp hair, erythema multiforme, erythema nodosum, hemorrhagic eruption, itching, and dizziness.

The following laboratory results may be altered by the use of estrogen-progestin combination drugs: increased sulfobromophthalein retention and other hepatic function tests; coagulation tests: increase in prothrombin factors VII, VIII, IX, and X; metyrapone test; pregnanediol determinations; thyroid function: increase in PBI and butanol extractable protein bound iodine, and decrease in T^3 uptake values.

DOSAGE AND ADMINISTRATION

Progesterone is administered by intramuscular injection. It differs from other commonly used steroids in that it is irritating at the place of injection.

Amenorrhea: Five to 10 mg are given for six to eight consecutive days. If there has been sufficient ovarian activity to produce a proliferative endometrium, one can expect withdrawal bleeding forty-eight to seventy-two hours after the last injection. This may be followed by spontaneous normal cycles.

Functional Uterine Bleeding: Five to 10 mg are given daily for six doses. Bleeding may be expected to cease within six days. When estrogen is given as well, the administration of progesterone is begun after two weeks of estrogen therapy. If menstrual flow begins during the course of injections of progesterone, they are discontinued.

Parenteral drug products should be inspected visually for particulate matter and discoloration prior to administration whenever the solution and container permit.

HOW SUPPLIED

Progesterone Injection USP, 500 mg/10 mL (50 mg/mL) is available in 10 mL multiple dose vials, individually boxed.

(NDC 0591-3128-79)

Store at 20°-25°C (68°-77°F). [See USP controlled room temperature.]

Rx only

For all medical inquiries contact:
ACTAVIS
Medical Communications
Parsippany, NJ 07054
800-272-5525
Distributed By:
Actavis Pharma, Inc.
Parsippany, NJ 07054 USA

Manufactured By:
Hikma Farmacêutica
Fervença 2705-906 Terrugem SNT
Portugal

Revised:August 2018

PATIENT INFORMATION

FOR THE TREATMENT OF AMENORRHEA (ABSENCE OF MENSES IN WOMEN WHO HAVE PREVIOUSLY HAD A MENSTRUAL PERIOD) OR ABNORMAL UTERINE BLEEDING DUE TO HORMONAL IMBALANCE.

Please read this information carefully before you start to use Progesterone Injection and each time your prescription is renewed, in case anything has changed. This leaflet does not take the place of discussions with your doctor. If you still have any questions, ask your doctor or health-care provider.

About Progesterone Injection
Progesterone Injection is a sterile injectable solution containing the natural female hormone called progesterone. Progesterone Injection is indicated for the treatment of amenorrhea and abnormal uterine bleeding due to progesterone deficiency.

Understanding the role of Progesterone Injection in the treatment of your menstrual irregularities.
Progesterone is one of the hormones essential for regular menstrual periods. If your doctor has determined your body does not produce enough progesterone on its own, Progesterone Injection may be prescribed to provide the progesterone you need.

When you do not produce enough progesterone, menstrual irregularities can occur. Progesterone Injection can provide you with the progesterone needed during a normal menstrual cycle.

Possible side effects of Progesterone Injection
The following side effects have been reported with Progesterone Injection. Consult your doctor if you experience any of the side effects mentioned below, or other side effects.

- anaphylactoid (life-threatening allergic) reaction with symptoms that may include a sense of uneasiness or apprehension; flushing; fast, throbbing heartbeat; itching; hives; difficult breathing; swelling of the throat; eosinophilic pneumonia (gathering of eosinophils, a type of white blood cell, in the lungs), fainting; nausea; vomiting; or convulsions.
- breakthrough bleeding
- spotting
- changes in menstrual flow
- amenorrhea
- change in weight (increase or decrease)
- pain, irritation, swelling, and/or redness at the injection area
- general swelling
- vaginal discharge
- yellow discoloration of skin or white of eyes
- breast tenderness, discharge from the nipple
- skin reactions including rash, hives, itching, and swelling
- acne
- hair loss or growth of new hair
- mental depression
- fever
- insomnia or sleepiness*
- nausea

*If you experience sleepiness, do not drive or operate machinery.

When you should not use Progesterone Injection

- If you are allergic to progesterone, progesterone-like drugs, benzyl alcohol or sesame oil/seeds.
- If you have unusual vaginal bleeding which has not been evaluated by your doctor.
- If you have liver disease.
- If you have known or suspected cancer of the breast or genital organs.
- If you have a miscarriage and your physician suspects some tissue is still in the uterus.
- If you have or have had blood clots in the legs, lungs, eyes, or elsewhere.

Risks of Progesterone Injection

- Abnormal blood clotting. Blood clots have been reported with the use of estrogens and progestational drugs (alone or in combination). If blood clots do form in your bloodstream, they can cut off the blood supply to vital organs, causing serious problems. These problems may include a stroke (by cutting off blood to part of the brain), a heart attack (by cutting off blood to part of the heart), a pulmonary embolus (by cutting off blood to part of the lungs), or other problems. Any of these conditions may cause death or serious long-term disability. Call your doctor immediately if you suspect you have any of these conditions. He or she may advise you to stop using this drug.

Precautions
Be alert for unusual signs and symptoms. If any of these warning signals (or any other unusual symptoms) happen while you are using Progesterone Injection, call your doctor immediately:

- Abnormal bleeding from the vagina.
- Pains in the calves or chest, a sudden shortness of breath or coughing blood indicating possible clots in the legs, heart, or lungs.
- Severe headache or vomiting, dizziness, faintness, or changes in vision or speech, weakness or numbness of an arm or leg indicating possible clots in the brain or eye.
- Breast lumps, which could be associated with fibrocystic disorders, fibroadenoma, or breast cancer. (Ask your doctor or health-care provider to show you how to examine your breasts monthly.)
- Yellowing of the skin and/or white of the eyes indicating possible liver problems.

How Progesterone Injection works
Progesterone Injection is intended for administration by injection into a muscle mass. Following injection, the medication is absorbed into the bloodstream.

Other information

- Your doctor has prescribed this drug for you and you alone. Do not give this drug to anyone else.
- This medication was prescribed for your particular medical condition. Do not use it for another condition.
- Keep this and all drugs out of the reach of children.

How to use Progesterone Injection
Progesterone Injection will be administered to you by a health-care provider or your caregiver. Your doctor will provide instructions regarding the dose and manner in which the medication should be injected. Follow your doctor’s instructions closely. If you have any questions about product administration, ask your doctor or health-care provider.

How Supplied
Progesterone Injection, 500 mg/10 mL (50 mg/mL) is available in 10 mL multiple dose vials. Vials are individually boxed.

Progesterone Injection should be stored at 20°-25°C (68°-77°F). [See USP controlled room temperature.]

Do not use Progesterone Injection after the expiration date which is printed on the vial label.

Rx only

For all medical inquiries contact:
ACTAVIS
Medical Communications
Parsippany, NJ 07054
800-272-5525

Distributed By:
Actavis Pharma, Inc.
Parsippany, NJ 07054 USA

Manufactured By:
Hikma Farmacêutica
Fervença 2705-906 Terrugem SNT
Portugal

Revised:August 2018

PRINCIPAL DISPLAY PANEL

Actavis Rx Only

NDC 0591-3128-79

Progesterone Injection USP

500 mg/10 mL (50 mg/mL)

For intramuscular use only

Contains 10 mL Multiple Dose Vial